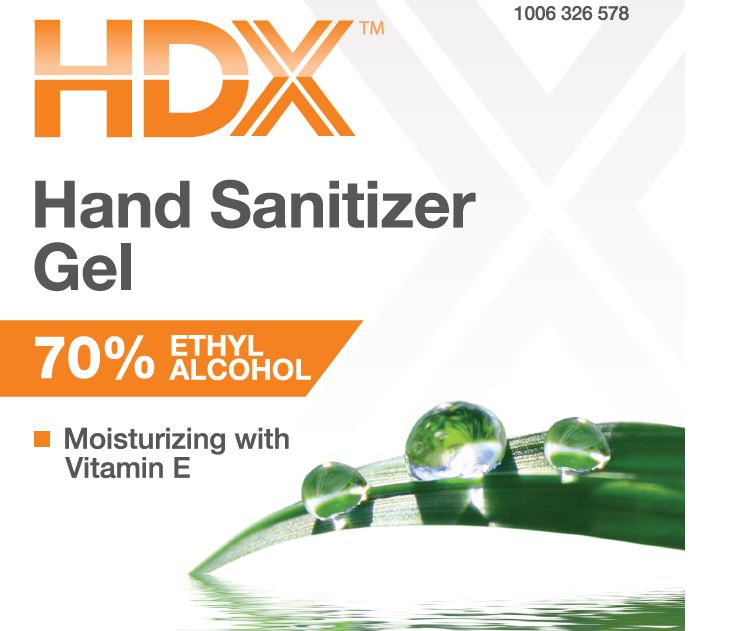 DRUG LABEL: Hand Sanitizer Gel
NDC: 66949-137 | Form: LIQUID
Manufacturer: Zep Inc.
Category: otc | Type: HUMAN OTC DRUG LABEL
Date: 20251226

ACTIVE INGREDIENTS: ALCOHOL 70 mL/100 mL
INACTIVE INGREDIENTS: ALPHA-TOCOPHEROL ACETATE; WATER; TRIISOPROPANOLAMINE; ACRYLATES CROSSPOLYMER-6

66949-137 / 4508 HDX Hand Sanitizer Gel

Active ingredient

Ethanol 70% v/v

Purpose

Antiseptic

Uses

■ To help reduce bacteria that can potentially cause disease

■ For use when soap and water are not available

Warnings

For external use only.

Flammable. Keep away from source of heat or fire

Do Not Use

■ on children less than 2 months of age

■ on open skin wounds

■ on broken or damaged skin

When using this product avoid contact with eyes. If contact occurs, rinse eyes thoroughly with water. Do not inhale.

Stop use and ask a doctor if irritation or redness develops and lasts.

Keep out of reach of children and pets. In case of accidental ingestion, get medical help or contact a Poison Control Center immediately.

Directions

■ For occasional and personal use.

■ Rub thoroughly into hands for at least 30 seconds. Allow to dry.

■ Children under 6 years should be supervised when using this product.

Other information

■ store at a temperature below 110 °F (43 °C).

■ may discolor certain fabrics or surfaces.

Inactive ingredients

Water, Triisopropanolamine, Acrylates/C10-30 Alkyl Acrylate Crosspolymer, Tocopheryl Acetate.

Questions?

1-800-514-6729